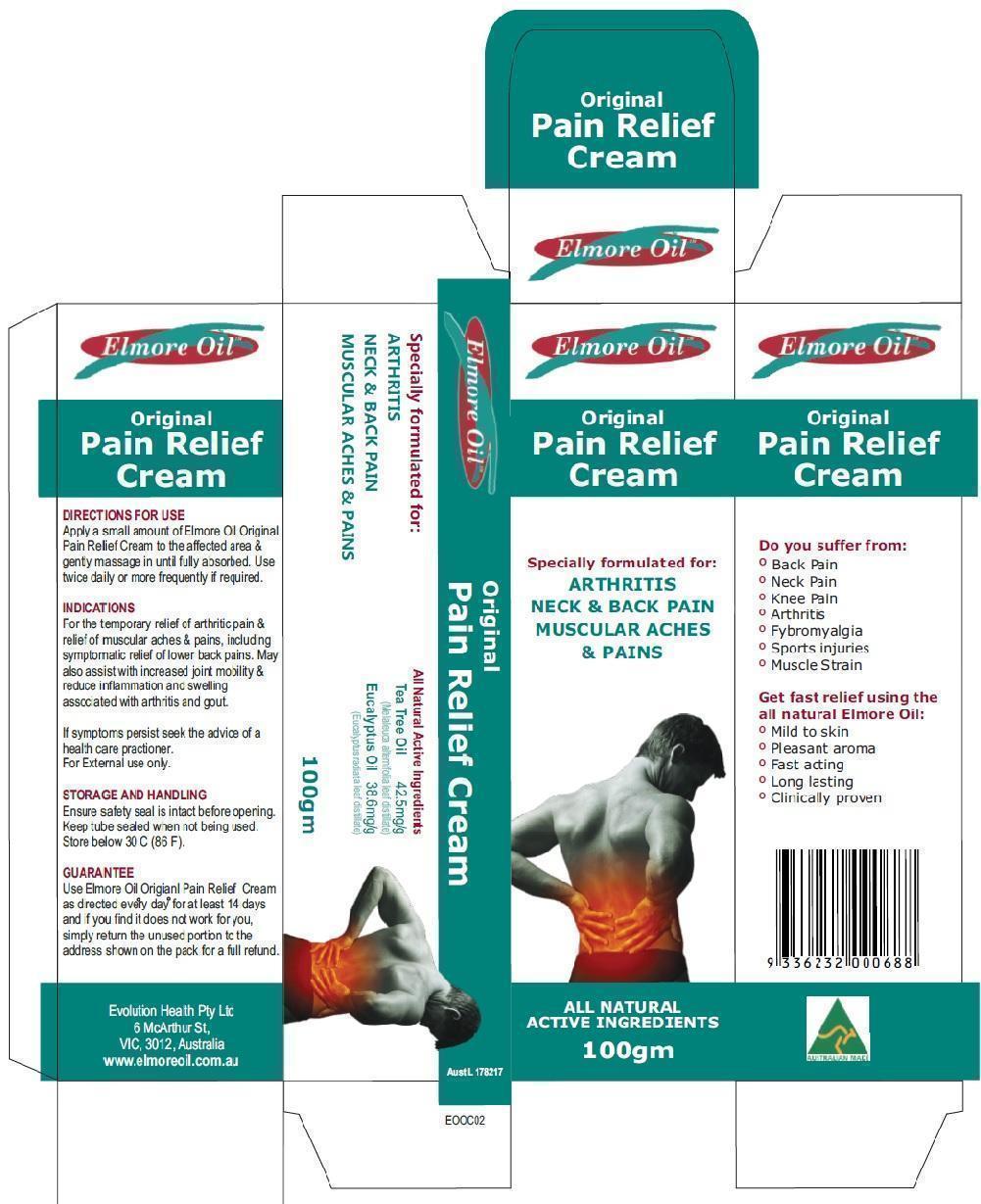 DRUG LABEL: Original Pain Relief Cream
NDC: 69594-004 | Form: CREAM
Manufacturer: Ultra Mix (Aust) Pty Ltd 
Category: prescription | Type: HUMAN PRESCRIPTION DRUG LABEL
Date: 20150216

ACTIVE INGREDIENTS: EUCALYPTUS OIL 38.6 mg/1 g; TEA TREE OIL 42.5 mg/1 g

Original Pain Relief Cream

Actives

Tea Tree Oil (Melaleuca Alternifolia) - 42.5 mg/g
Eucalyptus Oil (Eucalyptus radiata) - 38.6 mg/g

Purpose

Pain relief cream to assist with relief of joint and muscle pain.

Indication and Usage

For the temporary relief of arthritic pain & relief of muscular aches & pains, including symptomatic relief of lower back pains. May

also assist with increased joint mobility & reduce inflammation and swelling associated with arthritis and gout.

Dosage and Administration

Apply a small amount of Original Pain Relief Cream to the affected area & gently massage in until fully absorbed. Use

twice daily or more frequently if required.

Warnings

For external use only.

Ensure safety seal is intact beforeopening. Keep tube sealed when not being used. Store below 30^0 C (86 F).

If symptoms persist seek the advice of a health care practioner.

Keep out of reach from children.